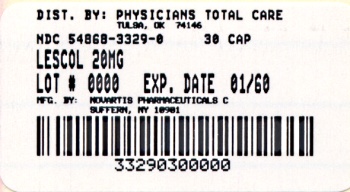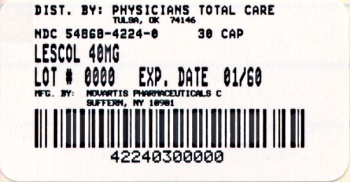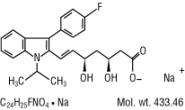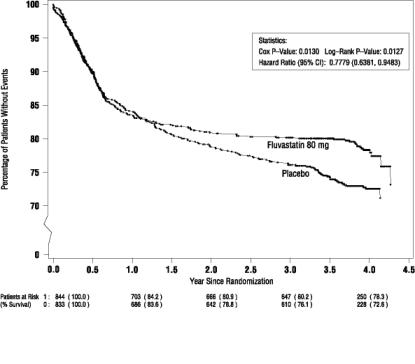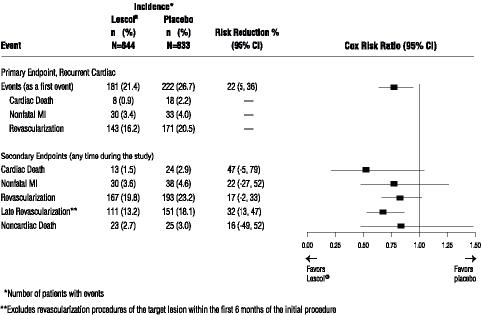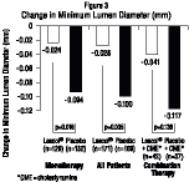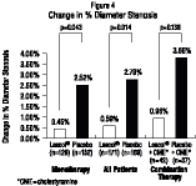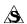 DRUG LABEL: LESCOL
NDC: 54868-3329 | Form: CAPSULE
Manufacturer: Physicians Total Care, Inc.
Category: prescription | Type: HUMAN PRESCRIPTION DRUG LABEL
Date: 20110323

ACTIVE INGREDIENTS: FLUVASTATIN SODIUM 20 mg/1 1
INACTIVE INGREDIENTS: BENZYL ALCOHOL; FERROSOFERRIC OXIDE; BUTYLPARABEN; CARBOXYMETHYLCELLULOSE SODIUM; EDETATE CALCIUM DISODIUM; GELATIN; MAGNESIUM STEARATE; METHYLPARABEN; CELLULOSE, MICROCRYSTALLINE; STARCH, CORN; PROPYLPARABEN; FERRIC OXIDE RED; SILICON DIOXIDE; SODIUM LAURYL SULFATE; SODIUM PROPIONATE; TALC; TITANIUM DIOXIDE; FERRIC OXIDE YELLOW; CALCIUM CARBONATE; SODIUM BICARBONATE

Lescol®

(fluvastatin sodium)

Capsules

Lescol® XL

(fluvastatin sodium)

Extended-Release Tablets

Rx only

Prescribing Information

DESCRIPTION

Lescol® (fluvastatin sodium), is a water-soluble cholesterol lowering agent which acts through the inhibition of 3-hydroxy-3-methylglutaryl-coenzyme A (HMG-CoA) reductase.

Fluvastatin sodium is [R*,S*-(E)]-(±)-7-[3-(4-fluorophenyl)-1-(1-methylethyl)-1H-indol-2-yl]-3,5-dihydroxy-6-heptenoic acid, monosodium salt. The empirical formula of fluvastatin sodium is C24H25FNO4•Na, its molecular weight is 433.46 and its structural formula is:

This molecular entity is the first entirely synthetic HMG-CoA reductase inhibitor, and is in part structurally distinct from the fungal derivatives of this therapeutic class.

Fluvastatin sodium is a white to pale yellow, hygroscopic powder soluble in water, ethanol and methanol. Lescol is supplied as capsules containing fluvastatin sodium, equivalent to 20 mg or 40 mg of fluvastatin, for oral administration. Lescol® XL (fluvastatin sodium) is supplied as extended-release tablets containing fluvastatin sodium, equivalent to 80 mg of fluvastatin, for oral administration.

Active Ingredient: fluvastatin sodium

Inactive Ingredients in capsules: gelatin, magnesium stearate, microcrystalline cellulose, pregelatinized starch (corn), red iron oxide, sodium lauryl sulfate, talc, titanium dioxide, yellow iron oxide, and other ingredients.

Capsules may also include: benzyl alcohol, black iron oxide, butylparaben, carboxymethylcellulose sodium, edetate calcium disodium, methylparaben, propylparaben, silicon dioxide and sodium propionate.

Inactive Ingredients in extended-release tablets: microcrystalline cellulose, hydroxypropyl cellulose, hydroxypropyl methyl cellulose, potassium bicarbonate, povidone, magnesium stearate, yellow iron oxide, titanium dioxide and polyethylene glycol 8000.

CLINICAL PHARMACOLOGY

A variety of clinical studies have demonstrated that elevated levels of total cholesterol (Total-C), low density lipoprotein cholesterol (LDL-C), triglycerides (TG) and apolipoprotein B (a membrane transport complex for LDL-C) promote human atherosclerosis. Similarly, decreased levels of HDL-cholesterol (HDL-C) and its transport complex, apolipoprotein A, are associated with the development of atherosclerosis. Epidemiologic investigations have established that cardiovascular morbidity and mortality vary directly with the level of Total-C and LDL-C and inversely with the level of HDL-C.

Like LDL, cholesterol-enriched triglyceride-rich lipoproteins, including VLDL, IDL and remnants, can also promote atherosclerosis. Elevated plasma triglycerides are frequently found in a triad with low HDL-C levels and small LDL particles, as well as in association with non-lipid metabolic risk factors for coronary heart disease. As such, total plasma TG has not consistently been shown to be an independent risk factor for CHD. Furthermore, the independent effect of raising HDL or lowering TG on the risk of coronary and cardiovascular morbidity and mortality has not been determined.

In patients with hypercholesterolemia and mixed dyslipidemia, treatment with Lescol® (fluvastatin sodium) or Lescol® XL (fluvastatin sodium) reduced Total-C, LDL-C, apolipoprotein B, and triglycerides while producing an increase in HDL-C. Increases in HDL-C are greater in patients with low HDL-C (<35 mg/dL). Neither agent had a consistent effect on either Lp(a) or fibrinogen. The effect of Lescol or Lescol XL induced changes in lipoprotein levels, including reduction of serum cholesterol, on cardiovascular mortality has not been determined.

Mechanism of Action

Lescol is a competitive inhibitor of HMG-CoA reductase, which is responsible for the conversion of 3-hydroxy-3-methylglutaryl-coenzyme A (HMG-CoA) to mevalonate, a precursor of sterols, including cholesterol. The inhibition of cholesterol biosynthesis reduces the cholesterol in hepatic cells, which stimulates the synthesis of LDL receptors and thereby increases the uptake of LDL particles. The end result of these biochemical processes is a reduction of the plasma cholesterol concentration.

Pharmacokinetics/Metabolism Oral Absorption

Fluvastatin is absorbed rapidly and completely following oral administration of the capsule, with peak concentrations reached in less than 1 hour. Following administration of a 10 mg dose, the absolute bioavailability is 24% (range 9%-50%). Administration with food reduces the rate but not the extent of absorption. At steady state, administration of fluvastatin with the evening meal results in a two-fold decrease in Cmax and more than two-fold increase in tmax as compared to administration 4 hours after the evening meal. No significant differences in extent of absorption or in the lipid-lowering effects were observed between the two administrations. After single or multiple doses above 20 mg, fluvastatin exhibits saturable first-pass metabolism resulting in higher than expected plasma fluvastatin concentrations.

Fluvastatin has two optical enantiomers, an active 3R,5S and an inactive 3S,5R form. In vivo studies showed that stereo-selective hepatic binding of the active form occurs during the first pass resulting in a difference in the peak levels of the two enantiomers, with the active to inactive peak concentration ratio being about 0.7. The approximate ratio of the active to inactive approaches unity after the peak is seen and thereafter the two enantiomers decline with the same half-life. After an intravenous administration, bypassing the first-pass, metabolism, the ratios of the enantiomers in plasma were similar throughout the concentration-time profiles.

Fluvastatin administered as Lescol XL 80 mg tablets reaches peak concentration in approximately 3 hours under fasting conditions, after a low-fat meal, or 2.5 hours after a low-fat meal. The mean relative bioavailability of the XL tablet is approximately 29% (range: 9%-66%) compared to that of the Lescol immediate-release capsule administered under fasting conditions. Administration of a high-fat meal delayed the absorption (Tmax: 6H) and increased the bioavailability of the XL tablet by approximately 50%. Once Lescol XL begins to be absorbed, fluvastatin concentrations rise rapidly. The maximum concentration seen after a high-fat meal is much less than the peak concentration following a single dose or twice daily dose of the 40 mg Lescol capsule. Overall variability in the pharmacokinetics of Lescol XL is large (42%-64% CV for Cmax and AUC), and especially so after a high-fat meal (63%-89% for Cmax and AUC). Intrasubject variability in the pharmacokinetics of Lescol XL under fasting conditions (about 25% for Cmax and AUC) tends to be much smaller as compared to the overall variability. Multiple peaks in plasma fluvastatin concentrations have been observed after Lescol XL administration.

Distribution

Fluvastatin is 98% bound to plasma proteins. The mean volume of distribution (VDss) is estimated at 0.35 L/kg. The parent drug is targeted to the liver and no active metabolites are present systemically. At therapeutic concentrations, the protein binding of fluvastatin is not affected by warfarin, salicylic acid and glyburide.

Metabolism

Fluvastatin is metabolized in the liver, primarily via hydroxylation of the indole ring at the 5- and 6-positions. N-dealkylation and beta-oxidation of the side-chain also occurs. The hydroxy metabolites have some pharmacologic activity, but do not circulate in the blood. Both enantiomers of fluvastatin are metabolized in a similar manner.

In vitro studies demonstrated that fluvastatin undergoes oxidative metabolism, predominantly via 2C9 isozyme systems (75%). Other isozymes that contribute to fluvastatin metabolism are 2C8 (~5%) and 3A4 (~20%). (See PRECAUTIONS: Drug Interactions Section).

Elimination

Fluvastatin is primarily (about 90%) eliminated in the feces as metabolites, with less than 2% present as unchanged drug. Urinary recovery is about 5%. After a radiolabeled dose of fluvastatin, the clearance was 0.8 L/h/kg. Following multiple oral doses of radiolabeled compound, there was no accumulation of fluvastatin; however, there was a 2.3- fold accumulation of total radioactivity.

Steady-state plasma concentrations show no evidence of accumulation of fluvastatin following immediate release capsule administration of up to 80 mg daily, as evidenced by a beta-elimination half-life of less than 3 hours. However, under conditions of maximum rate of absorption (i.e., fasting) systemic exposure to fluvastatin is increased 33% to 53% compared to a single 20 mg or 40 mg dose of the immediate- release capsule. Following once daily administration of the 80 mg Lescol XL tablet for 7 days, systemic exposure to fluvastatin is increased (20%-30%) compared to a single dose of the 80 mg Lescol XL tablet. Terminal half-life of Lescol XL was about 9 hours as a result of the slow-release formulation.

Single-dose and steady-state pharmacokinetic parameters in 33 subjects with hypercholesterolemia for the capsules and in 35 healthy subjects for the extended-release tablets are summarized below:

Table 1 Single-Dose and Steady-State Pharmacokinetic Parameters
 |  | Cmax (ng/mL) mean±SD (range) | AUC (ng·h/mL) mean±SD (range) | tmax (hr) mean±SD (range) | CL/F (L/hr) mean±SD (range) | t 1/2 (hr) mean±SD (range)
Capsules
 | 20 mg single dose (n=17) | 166±106 | 207±65 | 0.9±0.4 | 107±38.1 | 2.5±1.7
 |  | (48.9-517) | (111-288) | (0.5-2.0) | (69.5-181) | (0.5-6.6)
 | 20 mg twice daily (n=17) | 200±86 | 275±111 | 1.2±0.9 | 87.8±45 | 2.8±1.7
 |  | (71.8-366) | (91.6-467) | (0.5-4.0) | (42.8-218) | (0.9-6.0)
 | 40 mg single dose (n=16) | 273±189 | 456±259 | 1.2±0.7 | 108±44.7 | 2.7±1.3
 |  | (72.8-812) | (207-1221) | (0.75-3.0) | (32.8-193) | (0.8-5.9)
 | 40 mg twice daily (n=16) | 432±236 | 697±275 | 1.2±0.6 | 64.2±21.1 | 2.7±1.3
 |  | (119-990) | (359-1559) | (0.5-2.5) | (25.7-111) | (0.7-5.0)
Extended-Release Tablets 80 mg single dose (n=24)
 | 80 mg single dose, fasting (n=24) | 126±53 | 579±341 | 3.2± 2.6 | - | -
 |  | (37-242) | (144-1760) | (1-12)
 | 80 mg single dose, fed state high- fat meal (n=-24) | 183±163 | 861±632 | 6 | - | -
 |  | (21-733) | (199-3132) | (2-24)
Extended-Release Tablets 80 mg following 7 days dosing (steady-state) (n=11)
 | 80 mg once daily, fasting (n=11) | 102±42 | 630±326 | 2.6±0.91 | - | -
 |  | (43.9-181) | (247-1406) | (1.5-4)

Special Populations Renal Insufficiency:

No significant (<6%) renal excretion of fluvastatin occurs in humans.

Hepatic Insufficiency:

Fluvastatin is subject to saturable first-pass metabolism/sequestration by the liver and is eliminated primarily via the biliary route. Therefore, the potential exists for drug accumulation in patients with hepatic insufficiency. Caution should therefore be exercised when fluvastatin sodium is administered to patients with a history of liver disease or heavy alcohol ingestion (see WARNINGS).

Fluvastatin AUC and Cmax values increased by about 2.5- fold in hepatic insufficiency patients. This result was attributed to the decreased presystemic metabolism due to hepatic dysfunction. The enantiomer ratios of the two isomers of fluvastatin in hepatic insufficiency patients were comparable to those observed in healthy subjects.

Age:

Plasma levels of fluvastatin are not affected by age.

Gender:

Women tend to have slightly higher (but statistically insignificant) fluvastatin concentrations than men for the immediate- release capsule. This is most likely due to body weight differences, as adjusting for body weight decreases the magnitude of the differences seen. For Lescol XL, there are 67% and 77% increases in systemic availability for women over men under fasted and high- fat meal conditions.

Pediatric:

Pharmacokinetic data in the pediatric population are not available.

CLINICAL STUDIES

Hypercholesterolemia (heterozygous familial and nonfamilial) and Mixed Dyslipidemia

In 12 placebo-controlled studies in patients with Type IIa or IIb hyperlipoproteinemia, Lescol® (fluvastatin sodium) alone was administered to 1621 patients in daily dose regimens of 20 mg, 40 mg, and 80 mg (40 mg twice daily) for at least 6 weeks duration. After 24 weeks of treatment, daily doses of 20 mg, 40 mg, and 80 mg (40 mg twice daily) resulted in median LDL-C reductions of 22% (n=747), 25% (n=748) and 36% (n=257), respectively. Lescol treatment produced dose-related reductions in Apo B and in triglycerides and increases in HDL-C. The median (25th, 75th percentile) percent changes from baseline in HDL-C after 12 weeks of treatment with Lescol at daily doses of 20 mg, 40 mg and 80 mg (40 mg twice daily) were +2 (-4,+10), +5 (-2,+12), and +4 (-3,+12), respectively. In a subgroup of patients with primary mixed dyslipidemia, defined as baseline TG levels >200 mg/dL, treatment with Lescol also produced significant decreases in Total-C, LDL-C, TG and Apo B and variable increases in HDL-C. The median (25th, 75th percentile) percent changes from baseline in HDL-C after 12 weeks of treatment with Lescol at daily doses of 20 mg, 40 mg and 80 mg (40 mg twice daily) in this population were +4 (-2,+12), +8 (+1,+15), and +4 (-3,+13), respectively.

In a long-term open-label free titration study, after 96 weeks LDL-C decreases of 25% (20 mg, n=68), 31% (40 mg, n=298) and 34% (80 mg, n=209) were seen. No consistent effect on Lp(a) was observed.

Lescol® XL (fluvastatin sodium) Extended-Release Tablets have been studied in five controlled studies of patients with Type IIa or IIb hyperlipoproteinemia. Lescol XL was administered to over 900 patients in trials from 4 to 26 weeks in duration. In the three largest of these studies, Lescol XL given as a single daily dose of 80 mg significantly reduced Total-C, LDL-C, TG and Apo B. Therapeutic response is well established within two weeks, and a maximum response is achieved within four weeks. After four weeks of therapy, the median decrease in LDL-C was 38% and at Week 24 endpoint the median LDL-C decrease was 35%. Significant increases in HDL-C were also observed. The median (25th and 75th percentile) percent changes from baseline in HDL-C for Lescol XL were +7(+0,+15) after 24 weeks of treatment.

Table 2 Median Percent Change in Lipid Parameters from Baseline to Week 24 Endpoint All Placebo-Controlled Studies (Lescol®) and Active Controlled Trials (Lescol® XL)
 | Total Chol. | TG | LDL | Apo B | HDL
Dose | N | % ∆ | N | % ∆ | N | % ∆ | N | % ∆ | N | % ∆
All Patients
Lescol 20 mg^1 | 747 | -17 | 747 | -12 | 747 | -22 | 114 | -19 | 747 | +3
Lescol 40 mg^1 | 748 | -19 | 748 | -14 | 748 | -25 | 125 | -18 | 748 | +4
Lescol 40 mg twice daily^1 | 257 | -27 | 257 | -18 | 257 | -36 | 232 | -28 | 257 | +6
Lescol XL 80 mg^2 | 750 | -25 | 750 | -19 | 748 | -35 | 745 | -27 | 750 | +7
Baseline TG ≥200 mg/dL
Lescol 20 mg^1 | 148 | -16 | 148 | -17 | 148 | -22 | 23 | -19 | 148 | +6
Lescol 40 mg^1 | 179 | -18 | 179 | -20 | 179 | -24 | 47 | -18 | 179 | +7
Lescol 40 mg twice daily^1 | 76 | -27 | 76 | -23 | 76 | -35 | 69 | -28 | 76 | +9
Lescol XL 80 mg^2 | 239 | -25 | 239 | -25 | 237 | -33 | 235 | -27 | 239 | +11

^1 Data for Lescol from 12 placebo^- controlled trials

^2 Data for Lescol XL 80 mg tablet from three 24^- week controlled trials

In patients with primary mixed dyslipidemia (Fredrickson Type IIb) as defined by baseline plasma triglycerides levels >200 mg/dL, Lescol XL 80 mg produced a median reduction in triglycerides of 25%. In these patients, Lescol XL 80 mg produced median (25th and 75th percentile) percent change from baseline in HDL-C of +11(+3,+20). Significant decreases in Total-C, LDL-C, and Apo B were also achieved. In these studies, patients with triglycerides >400 mg/dL were excluded.

Heterozygous Familial Hypercholesterolemia in Pediatric Patients

Fluvastatin sodium was studied in two open-label, uncontrolled, dose-titration studies which enrolled pediatric patients with heterozygous familial hypercholesterolemia. The first study enrolled 29 pre-pubertal boys, 9-12 years of age, who had an LDL-C level > 90th percentile for age and one parent with primary hypercholesterolemia and either a family history of premature ischemic heart disease or tendon xanthomas. The mean baseline LDL-C was 226 mg/dL (range: 137-354 mg/dL). All patients were started on Lescol capsules 20 mg daily with dose adjustments every 6 weeks to 40 mg daily then 80 mg daily (40 mg bid) to achieve an LDL-C goal of 96.7 to 123.7 mg/dL. Endpoint analyses were performed at Year 2. The second study enrolled 85 male and female patients, 10 to 16 years of age, who had an LDL-C > 190 mg/dL or LDL-C > 160 mg/dL and one or more risk factors for coronary heart disease, or LDL-C > 160 mg/dL and a proven LDL-receptor defect. The mean baseline LDL-C was 225 mg/dL (range: 148-343 mg/dL). All patients were started on Lescol capsules 20 mg daily with dose adjustments every 6 weeks to 40 mg daily then 80 mg daily (Lescol 80 mg XL tablet) to achieve an LDL-C goal of < 130 mg/dL. Endpoint analyses were performed at Week 114.

In the first study, Lescol 20 mg to 80 mg daily doses decreased plasma levels of Total-C and LDL-C by 21% and 27%, respectively. The mean achieved LDL-C was 161 mg/dL (range: 74-336 mg/dL). In the second study, Lescol 20 mg to 80 mg daily doses decreased plasma levels of Total-C and LDL-C by 22% and 28%, respectively. The mean achieved LDL-C was 159 mg/dL (range: 90-295 mg/dL).

The majority of patients in both studies (83% in the first study and 89% in the second study) were titrated to the maximum daily dose of 80 mg. At study endpoint, 26 % to 30% of patients in both studies achieved a targeted LDL-C goal of < 130 mg/dL. The long-term efficacy of Lescol or Lescol XL therapy in childhood to reduce morbidity and mortality in adulthood has not been established.

Reduction in the Risk of Recurrent Cardiac Events

In the Lescol Intervention Prevention Study, the effect of Lescol 40 mg administered twice daily on the risk of recurrent cardiac events (time to first occurrence of cardiac death, nonfatal myocardial infarction, or revascularization) was assessed in 1677 patients with coronary heart disease who had undergone a percutaneous coronary intervention (PCI) procedure (mean time from PCI to randomization=3 days). In this multicenter, randomized, double-blind, placebo-controlled study, patients were treated with dietary/lifestyle counseling and either Lescol 40 mg (n=844) or placebo (n=833) given twice daily for a median of 3.9 years. The study population was 84% male, 98% Caucasian, with 37% >65 years of age. At baseline patients had total cholesterol between 100 and 367 mg/dL (mean 201 mg/dL), LDL-C between 42 and 243 mg/dL (mean 132 mg/dL), triglycerides between 15 and 270 mg/dL (mean 70 mg/dL) and HDL-C between 8 and 174 mg/dL (mean 39 mg/dL).

Lescol significantly reduced the risk of recurrent cardiac events (Figure 1) by 22% (p=0.013, 181 patients in the Lescol group vs. 222 patients in the placebo group). Revascularization procedures comprised the majority of the initial recurrent cardiac events (143 revascularization procedures in the Lescol group and 171 in the placebo group). Consistent trends in risk reduction were observed in patients >65 years of age.

Figure 1. Primary Endpoint – Recurrent Cardiac Events (Cardiac Death, Nonfatal MI or Revascularization Procedure) (ITT Population)

Outcome data for the Lescol Intervention Prevention Study are shown in Figure 2. After exclusion of revascularization procedures (CABG and repeat PCI) occurring within the first 6 months of the initial procedure involving the originally instrumental site, treatment with Lescol was associated with a 32% (p=0.002) reduction in risk of late revascularization procedures (CABG or PCI occurring at the original site >6 months after the initial procedure, or at another site).

Figure 2. Lescol® Intervention Prevention Study - Primary and Secondary Endpoints

Atherosclerosis

In the Lipoprotein and Coronary Atherosclerosis Study (LCAS), the effect of Lescol therapy on coronary atherosclerosis was assessed by quantitative coronary angiography (QCA) in patients with coronary artery disease and mild to moderate hypercholesterolemia (baseline LDL-C range 115-190 mg/dL). In this randomized double-blind, placebo- controlled trial, 429 patients were treated with conventional measures (Step 1 AHA Diet) and either Lescol 40 mg/day or placebo. In order to provide treatment to patients receiving placebo with LDL-C levels >160 mg/dL at baseline, adjunctive therapy with cholestyramine was added after Week 12 to all patients in the study with baseline LDL-C values of >160 mg/dL. These baseline levels were present in 25% of the study population. Quantitative coronary angiograms were evaluated at baseline and 2.5 years in 340 (79%) angiographic evaluable patients.

Lescol significantly slowed the progression of coronary atherosclerosis. Compared to placebo, Lescol significantly slowed the progression of lesions as measured by within-patient per-lesion change in minimum lumen diameter (MLD), the primary endpoint (see Figure 3 below), percent diameter stenosis (Figure 4), and the formation of new lesions (13% of all fluvastatin patients versus 22% of all placebo patients). Additionally, a significant difference in favor of Lescol was found between all fluvastatin and all placebo patients in the distribution among the three categories of definite progression, definite regression, and mixed or no change. Beneficial angiographic results (change in MLD) were independent of patients’ gender and consistent across a range of baseline LDL-C levels.

INDICATIONS AND USAGE

Therapy with lipid-altering agents should be used in addition to a diet restricted in saturated fat and cholesterol (see National Cholesterol Education Program [NCEP] Treatment Guidelines, below).

Hypercholesterolemia (heterozygous familial and nonfamilial) and Mixed Dyslipidemia

Lescol® (fluvastatin sodium) and Lescol® XL (fluvastatin sodium) are indicated to reduce elevated total cholesterol (Total-C), LDL-C, TG and Apo B levels, and to increase HDL-C in patients with primary hypercholesterolemia and mixed dyslipidemia (Fredrickson Type IIa and IIb) whose response to dietary restriction of saturated fat and cholesterol and other nonpharmacological measures has not been adequate.

Heterozygous Familial Hypercholesterolemia in Pediatric Patients

Lescol and Lescol XL are indicated as an adjunct to diet to reduce Total-C, LDL-C, and Apo B levels in adolescent boys and girls who are at least one year post-menarche, 10-16 years of age, with heterozygous familial hypercholesterolemia whose response to dietary restriction has not been adequate and the following findings are present:

1. LDL-C remains > 190 mg/dL or
2. LDL-C remains > 160 mg/dL and:
  - there is a positive family history of premature cardiovascular disease or
  - two or more other cardiovascular disease risk factors are present.

Therapy with lipid-altering agents should be considered only after secondary causes for hyperlipidemia such as poorly controlled diabetes mellitus, hypothyroidism, nephrotic syndrome, dysproteinemias, obstructive liver disease, other medication, or alcoholism, have been excluded. Prior to initiation of fluvastatin sodium, a lipid profile should be performed to measure Total-C, HDL-C and TG. For patients with TG <400 mg/dL (<4.5 mmol/L), LDL-C can be estimated using the following equation:

LDL-C = Total-C - HDL-C - 1/5 TG

For TG levels >400 mg/dL (>4.5 mmol/L), this equation is less accurate and LDL-C concentrations should be determined by ultracentrifugation. In many hypertriglyceridemic patients LDL-C may be low or normal despite elevated Total-C. In such cases, Lescol is not indicated.

Lipid determinations should be performed at intervals of no less than 4 weeks and dosage adjusted according to the patient’s response to therapy.

The National Cholesterol Education Program (NCEP) Treatment Guidelines are summarized below:

Table 3 NCEP Treatment Guidelines: LDL-C Goals and Cutpoints for Therapeutic Lifestyle Changes and Drug Therapy in Different Risk Categories
Risk Category | LDL Goal (mg/dL) | LDL Level at Which to Initiate Therapeutic Lifestyle Changes (mg/dL) | LDL Level at Which to Consider Drug Therapy (mg/dL)
CHD† or CHD risk equivalents (10-year risk >20%) | <100 | >100 | >130 (100-129: drug optional)††
2+ Risk factors (10-year risk <20%) | <130 | >130 | 10-year risk 10%-20%: >130 10-year risk <10%: >160
0-1 Risk factor††† | <160 | >160 | >190 (160-189: LDL-lowering drug optional)

† CHD, coronary heart disease

†† Some authorities recommend use of LDL-lowering drugs in this category if an LDL-C level of <100mg/dL cannot be achieved by therapeutic lifestyle changes. Others prefer use of drugs that primarily modify triglycerides and HDL-C, e.g., nicotinic acid or fibrate. Clinical judgement also may call for deferring drug therapy in this subcategory.

††† Almost all people with 0-1 risk factor have 10-year risk <10%; thus, 10-year risk assessment in people with 0-1 risk factor is not necessary.

After the LDL-C goal has been achieved, if the TG is still >200 mg/dL, non-HDL-C (Total-C minus HDL-C) becomes a secondary target of therapy. Non-HDL-C goals are set 30 mg/dL higher than LDL-C goals for each risk category.

At the time of hospitalization for an acute coronary event, consideration can be given to initiating drug therapy at discharge if the LDL-C level is >130 mg/dL (NCEP-ATP II).

Since the goal of treatment is to lower LDL-C, the NCEP recommends that the LDL-C levels be used to initiate and assess treatment response. Only if LDL-C levels are not available, should the Total-C be used to monitor therapy.

Table 4 Classification of Hyperlipoproteinemias
 |  | Lipid Elevations
Type | Lipoproteins Elevated | Major | Minor
I (rare) | Chylomicrons | TG | ↑→C
IIa | LDL | C | –
IIb | LDL, VLDL | C | TG
III (rare) | IDL | C/TG | –
IV | VLDL | TG | ↑→C
V (rare) | Chylomicrons, VLDL | TG | ↑→C

C = cholesterol, TG = triglycerides, LDL = low density lipoprotein, VLDL = very low density lipoprotein,

IDL = intermediate density lipoprotein

Neither Lescol nor Lescol XL have been studied in conditions where the major abnormality is elevation of chylomicrons, VLDL, or IDL (i.e., hyperlipoproteinemia Types I, III, IV, or V).

The NCEP classification of cholesterol levels in pediatric patients with a familial history of hypercholesterolemia or premature cardiovascular disease is summarized below:

Category | Total-C (mg/dL) | LDL-C (mg/dL)
Acceptable Borderline High | <170 170-199 >200 | <110 110-129 >130

Children treated with fluvastatin in adolescence should be re-evaluated in adulthood and appropriate changes made to their cholesterol-lowering regimen to achieve adult treatment goals.

Secondary Prevention of Coronary Events

In patients with coronary heart disease, Lescol and Lescol XL are indicated to reduce the risk of undergoing coronary revascularization procedures.

Atherosclerosis

Lescol and Lescol XL are also indicated to slow the progression of coronary atherosclerosis in patients with coronary heart disease as part of a treatment strategy to lower total and LDL cholesterol to target levels.

CONTRAINDICATIONS

Hypersensitivity to any component of this medication. Lescol® (fluvastatin sodium) and Lescol® XL (fluvastatin sodium) are contraindicated in patients with active liver disease or unexplained, persistent elevations in serum transaminases (see WARNINGS).

Pregnancy and Lactation

Atherosclerosis is a chronic process and discontinuation of lipid-lowering drugs during pregnancy should have little impact on the outcome of long-term therapy of primary hypercholesterolemia. Cholesterol and other products of cholesterol biosynthesis are essential components for fetal development (including synthesis of steroids and cell membranes). Since HMG-CoA reductase inhibitors decrease cholesterol synthesis and possibly the synthesis of other biologically active substances derived from cholesterol, they may cause fetal harm when administered to pregnant women. Therefore, HMG-CoA reductase inhibitors are contraindicated during pregnancy and in nursing mothers. Fluvastatin sodium should be administered to women of childbearing age only when such patients are highly unlikely to conceive and have been informed of the potential hazards. If the patient becomes pregnant while taking this class of drug, therapy should be discontinued and the patient apprised of the potential hazard to the fetus.

WARNINGS

Liver Enzymes

Biochemical abnormalities of liver function have been associated with HMG-CoA reductase inhibitors and other lipid-lowering agents. Approximately 1.1% of patients treated with Lescol® (fluvastatin sodium) capsules in worldwide trials developed dose-related, persistent elevations of transaminase levels to more than 3 times the upper limit of normal. Fourteen of these patients (0.6%) were discontinued from therapy. In all clinical trials, a total of 33/2969 patients (1.1%) had persistent transaminase elevations with an average fluvastatin exposure of approximately 71.2 weeks; 19 of these patients (0.6%) were discontinued. The majority of patients with these abnormal biochemical findings were asymptomatic.

In a pooled analysis of all placebo-controlled studies in which Lescol capsules were used, persistent transaminase elevations (>3 times the upper limit of normal [ULN] on two consecutive weekly measurements) occurred in 0.2%, 1.5%, and 2.7% of patients treated with 20, 40, and 80 mg (titrated to 40 mg twice daily) Lescol capsules, respectively. Ninety-one percent of the cases of persistent liver function test abnormalities (20 of 22 patients) occurred within 12 weeks of therapy and in all patients with persistent liver function test abnormalities there was an abnormal liver function test present at baseline or by Week 8.

In the pooled analysis of the 24-week controlled trials, persistent transaminase elevation occurred in 1.9%, 1.8% and 4.9% of patients treated with Lescol® XL (fluvastatin sodium) 80 mg, Lescol 40 mg and Lescol 40 mg twice daily, respectively. In 13 of 16 patients treated with Lescol XL the abnormality occurred within 12 weeks of initiation of treatment with Lescol XL 80 mg.

It is recommended that liver function tests be performed before the initiation of therapy and at 12 weeks following initiation of treatment or elevation in dose. Patients who develop transaminase elevations or signs and symptoms of liver disease should be monitored to confirm the finding and should be followed thereafter with frequent liver function tests until the levels return to normal. Should an increase in AST or ALT of three times the upper limit of normal or greater persist (found on two consecutive occasions) withdrawal of fluvastatin sodium therapy is recommended.

Active liver disease or unexplained transaminase elevations are contraindications to the use of Lescol and Lescol XL (see CONTRAINDICATIONS). Caution should be exercised when fluvastatin sodium is administered to patients with a history of liver disease or heavy alcohol ingestion (see CLINICAL PHARMACOLOGY: Pharmacokinetics/Metabolism). Such patients should be closely monitored.

Skeletal Muscle

Rhabdomyolysis with renal dysfunction secondary to myoglobinuria has been reported with fluvastatin and with other drugs in this class. Myopathy, defined as muscle aching or muscle weakness in conjunction with increases in creatine phosphokinase (CPK) values to greater than 10 times the upper limit of normal, has been reported.

Myopathy should be considered in any patients with diffuse myalgias, muscle tenderness or weakness, and/or marked elevation of CPK. Patients should be advised to report promptly unexplained muscle pain, tenderness or weakness, particularly if accompanied by malaise or fever. Fluvastatin sodium therapy should be discontinued if markedly elevated CPK levels occur or myopathy is diagnosed or suspected. Fluvastatin sodium therapy should also be temporarily withheld in any patient experiencing an acute or serious condition predisposing to the development of renal failure secondary to rhabdomyolysis, e.g., sepsis; hypotension; major surgery; trauma; severe metabolic, endocrine, or electrolyte disorders; or uncontrolled epilepsy.

The risk of myopathy and/or rhabdomyolysis during treatment with HMG-CoA reductase inhibitors has been reported to be increased if therapy with either cyclosporine, gemfibrozil, erythromycin, or niacin is administered concurrently. Isolated cases of myopathy have been reported during post-marketing experience with concomitant administration of fluvastatin and colchicine. No information is available on the pharmacokinetic interaction between fluvastatin and colchicine. However, myotoxicity, including muscle pain and weakness and rhabdomyloysis, have been reported anecdotally with concomitant administration of colchicine.

Myopathy was not observed in a clinical trial in 74 patients involving patients who were treated with fluvastatin sodium together with niacin.

Uncomplicated myalgia has been observed infrequently in patients treated with Lescol at rates indistinguishable from placebo.

The use of fibrates alone may occasionally be associated with myopathy. The combined use of HMG-CoA reductase inhibitors and fibrates should generally be avoided.

PRECAUTIONS

General

Before instituting therapy with Lescol® (fluvastatin sodium) or Lescol® XL (fluvastatin sodium), an attempt should be made to control hypercholesterolemia with appropriate diet, exercise, and weight reduction in obese patients, and to treat other underlying medical problems (see INDICATIONS AND USAGE).

The HMG-CoA reductase inhibitors may cause elevation of creatine phosphokinase and transaminase levels (see WARNINGS and ADVERSE REACTIONS). This should be considered in the differential diagnosis of chest pain in a patient on therapy with fluvastatin sodium.

Homozygous Familial Hypercholesterolemia

HMG-CoA reductase inhibitors are reported to be less effective in patients with rare homozygous familial hypercholesterolemia, possibly because these patients have few functional LDL receptors.

Information for Patients

Patients should be advised to report promptly unexplained muscle pain, tenderness or weakness, particularly if accompanied by malaise or fever.

Women should be informed that if they become pregnant while receiving Lescol or Lescol XL the drug should be discontinued immediately to avoid possible harmful effects on a developing fetus from a relative deficit of cholesterol and biological products derived from cholesterol. In addition, Lescol or Lescol XL should not be taken during nursing. (See CONTRAINDICATIONS.)

Drug Interactions

The below listed drug interaction information is derived from studies using immediate- release fluvastatin. Similar studies have not been conducted using the Lescol XL tablet.

Immunosuppressive Drugs, Gemfibrozil, Niacin (Nicotinic Acid), Erythromycin

(See WARNINGS: Skeletal Muscle).

In vitro data indicate that fluvastatin metabolism involves multiple Cytochrome P450 (CYP) isozymes. CYP2C9 isoenzyme is primarily involved in the metabolism of fluvastatin (~75%), while CYP2C8 and CYP3A4 isoenzymes are involved to a much less extent, i.e., ~5% and ~20%, respectively. If one pathway is inhibited in the elimination process of fluvastatin other pathways may compensate.

In vivo drug interaction studies with CYP3A4 inhibitors/substrates such as cyclosporine, erythromycin, and itraconazole result in minimal changes in the pharmacokinetics of fluvastatin, confirming less involvement of CYP3A4 isozyme. Concomitant administration of fluvastatin and phenytoin increased the levels of phenytoin and fluvastatin, suggesting predominant involvement of CYP2C9 in fluvastatin metabolism.

Niacin/Propranolol:

Concomitant administration of immediate- release fluvastatin sodium with niacin or propranolol has no effect on the bioavailability of fluvastatin sodium.

Cholestyramine:

Administration of immediate- release fluvastatin sodium concomitantly with, or up to 4 hours after cholestyramine, results in fluvastatin decreases of more than 50% for AUC and 50%-80% for Cmax. However, administration of immediate- release fluvastatin sodium 4 hours after cholestyramine resulted in a clinically significant additive effect compared with that achieved with either component drug.

Cyclosporine:

Plasma cyclosporine levels remain unchanged when fluvastatin (20 mg daily) was administered concurrently in renal transplant recipients on stable cyclosporine regimens. Fluvastatin AUC increased 1.9- fold, and Cmax increased 1.3- fold compared to historical controls.

Digoxin:

In a crossover study involving 18 patients chronically receiving digoxin, a single 40 mg dose of immediate- release fluvastatin had no effect on digoxin AUC, but had an 11% increase in digoxin Cmax and small increase in digoxin urinary clearance.

Erythromycin:

Erythromycin (500 mg, single dose) did not affect steady-state plasma levels of fluvastatin (40 mg daily).

Fluconazole:

Administration of fluvastatin 40 mg single dose to healthy volunteers pre-treated with fluconazole for 4 days results in an increase of fluvastatin Cmax (44%) and AUC (84%). Based on this data, caution should be exercised when fluvastatin is co-administered with fluconazole.

Itraconazole:

Concomitant administration of fluvastatin (40 mg) and itraconazole (100 mg daily x 4 days) does not affect plasma itraconazole or fluvastatin levels.

Gemfibrozil:

There is no change in either fluvastatin (20 mg twice daily) or gemfibrozil (600 mg twice daily) plasma levels when these drugs are co-administered.

Phenytoin:

Single morning dose administration of phenytoin (300 mg extended release) increased mean steady-state fluvastatin (40 mg) Cmax by 27% and AUC by 40% whereas fluvastatin increased the mean phenytoin Cmax by 5% and AUC by 20%. Patients on phenytoin should continue to be monitored appropriately when fluvastatin therapy is initiated or when the fluvastatin dosage is changed.

Diclofenac:

Concurrent administration of fluvastatin (40 mg) increased the mean Cmax and AUC of diclofenac by 60% and 25% respectively.

Tolbutamide:

In healthy volunteers, concurrent administration of either single or multiple daily doses of fluvastatin sodium (40 mg) with tolbutamide (1 g) did not affect the plasma levels of either drug to a clinically significant extent.

Glibenclamide (Glyburide):

In glibenclamide-treated NIDDM patients (n=32), administration of fluvastatin (40 mg twice daily for 14 days) increased the mean Cmax, AUC, and t1/2 of glibenclamide approximately 50%, 69% and 121%, respectively. Glibenclamide (5-20 mg daily) increased the mean Cmax and AUC of fluvastatin by 44% and 51%, respectively. In this study there were no changes in glucose, insulin and C-peptide levels. However, patients on concomitant therapy with glibenclamide (glyburide) and fluvastatin should continue to be monitored appropriately when their fluvastatin dose is increased to 40 mg twice daily.

Losartan:

Concomitant administration of fluvastatin with losartan has no effect on the bioavailability of either losartan or its active metabolite.

Cimetidine/Ranitidine/Omeprazole:

Concomitant administration of immediate- release fluvastatin sodium with cimetidine, ranitidine and omeprazole results in a significant increase in the fluvastatin Cmax (43%, 70% and 50%, respectively) and AUC (24%-33%), with an 18%-23% decrease in plasma clearance.

Rifampicin:

Administration of immediate- release fluvastatin sodium to subjects pretreated with rifampicin results in significant reduction in Cmax (59%) and AUC (51%), with a large increase (95%) in plasma clearance.

Warfarin:

In vitro protein binding studies demonstrated no interaction at therapeutic concentrations. Concomitant administration of a single dose of warfarin (30 mg) in young healthy males receiving immediate- release fluvastatin sodium (40 mg/day x 8 days) resulted in no elevation of racemic warfarin concentration. There was also no effect on prothrombin complex activity when compared to concomitant administration of placebo and warfarin. However, bleeding and/or increased prothrombin times have been reported in patients taking coumarin anticoagulants concomitantly with other HMG-CoA reductase inhibitors. Therefore, patients receiving warfarin-type anticoagulants should have their prothrombin times closely monitored when fluvastatin sodium is initiated or the dosage of fluvastatin sodium is changed.

Endocrine Function

HMG-CoA reductase inhibitors interfere with cholesterol synthesis and lower circulating cholesterol levels and, as such, might theoretically blunt adrenal or gonadal steroid hormone production.

Fluvastatin exhibited no effect upon non-stimulated cortisol levels and demonstrated no effect upon thyroid metabolism as assessed by TSH. Small declines in total testosterone have been noted in treated groups, but no commensurate elevation in LH occurred, suggesting that the observation was not due to a direct effect upon testosterone production. No effect upon FSH in males was noted. Due to the limited number of premenopausal females studied to date, no conclusions regarding the effect of fluvastatin upon female sex hormones may be made.

Two clinical studies in patients receiving fluvastatin at doses up to 80 mg daily for periods of 24 to 28 weeks demonstrated no effect of treatment upon the adrenal response to ACTH stimulation. A clinical study evaluated the effect of fluvastatin at doses up to 80 mg daily for 28 weeks upon the gonadal response to HCG stimulation. Although the mean total testosterone response was significantly reduced (p<0.05) relative to baseline in the 80 mg group, it was not significant in comparison to the changes noted in groups receiving either 40 mg of fluvastatin or placebo.

Patients treated with fluvastatin sodium who develop clinical evidence of endocrine dysfunction should be evaluated appropriately. Caution should be exercised if an HMG-CoA reductase inhibitor or other agent used to lower cholesterol levels is administered to patients receiving other drugs (e.g., ketoconazole, spironolactone, or cimetidine) that may decrease the levels of endogenous steroid hormones.

CNS Toxicity

CNS effects, as evidenced by decreased activity, ataxia, loss of righting reflex, and ptosis were seen in the following animal studies: the 18-month mouse carcinogenicity study at 50 mg/kg/day, the 6-month dog study at 36 mg/kg/day, the 6-month hamster study at 40 mg/kg/day, and in acute, high-dose studies in rats and hamsters (50 mg/kg), rabbits (300 mg/kg) and mice (1500 mg/kg). CNS toxicity in the acute high-dose studies was characterized (in mice) by conspicuous vacuolation in the ventral white columns of the spinal cord at a dose of 5000 mg/kg and (in rat) by edema with separation of myelinated fibers of the ventral spinal tracts and sciatic nerve at a dose of 1500 mg/kg. CNS toxicity, characterized by periaxonal vacuolation, was observed in the medulla of dogs that died after treatment for 5 weeks with 48 mg/kg/day; this finding was not observed in the remaining dogs when the dose level was lowered to 36 mg/kg/day. CNS vascular lesions, characterized by perivascular hemorrhages, edema, and mononuclear cell infiltration of perivascular spaces, have been observed in dogs treated with other members of this class. No CNS lesions have been observed after chronic treatment for up to 2 years with fluvastatin in the mouse (at doses up to 350 mg/kg/day), rat (up to 24 mg/kg/day), or dog (up to 16 mg/kg/day).

Prominent bilateral posterior Y suture lines in the ocular lens were seen in dogs after treatment with 1, 8, and 16 mg/kg/day for 2 years.

Carcinogenesis, Mutagenesis, Impairment of Fertility

A 2-year study was performed in rats at dose levels of 6, 9, and 18-24 (escalated after 1 year) mg/kg/day. These treatment levels represented plasma drug levels of approximately 9, 13, and 26-35 times the mean human plasma drug concentration after a 40 mg oral dose. A low incidence of forestomach squamous papillomas and 1 carcinoma of the forestomach at the 24 mg/kg/day dose level was considered to reflect the prolonged hyperplasia induced by direct contact exposure to fluvastatin sodium rather than to a systemic effect of the drug. In addition, an increased incidence of thyroid follicular cell adenomas and carcinomas was recorded for males treated with 18-24 mg/kg/day. The increased incidence of thyroid follicular cell neoplasm in male rats with fluvastatin sodium appears to be consistent with findings from other HMG-CoA reductase inhibitors. In contrast to other HMG-CoA reductase inhibitors, no hepatic adenomas or carcinomas were observed.

The carcinogenicity study conducted in mice at dose levels of 0.3, 15 and 30 mg/kg/day revealed, as in rats, a statistically significant increase in forestomach squamous cell papillomas in males and females at 30 mg/kg/day and in females at 15 mg/kg/day. These treatment levels represented plasma drug levels of approximately 0.05, 2, and 7 times the mean human plasma drug concentration after a 40 mg oral dose.

No evidence of mutagenicity was observed in vitro, with or without rat-liver metabolic activation, in the following studies: microbial mutagen tests using mutant strains of Salmonella typhimurium or Escherichia coli; malignant transformation assay in BALB/3T3 cells; unscheduled DNA synthesis in rat primary hepatocytes; chromosomal aberrations in V79 Chinese Hamster cells; HGPRT V79 Chinese Hamster cells. In addition, there was no evidence of mutagenicity in vivo in either a rat or mouse micronucleus test.

In a study in rats at dose levels for females of 0.6, 2 and 6 mg/kg/day and at dose levels for males of 2, 10 and 20 mg/kg/day, fluvastatin sodium had no adverse effects on the fertility or reproductive performance.

Seminal vesicles and testes were small in hamsters treated for 3 months at 20 mg/kg/day (approximately three times the 40 milligram human daily dose based on surface area, mg/m^2). There was tubular degeneration and aspermatogenesis in testes as well as vesiculitis of seminal vesicles. Vesiculitis of seminal vesicles and edema of the testes were also seen in rats treated for 2 years at 18 mg/kg/day (approximately 4 times the human Cmax achieved with a 40 milligram daily dose).

Pregnancy Pregnancy Category X

See CONTRAINDICATIONS.

Fluvastatin sodium produced delays in skeletal development in rats at doses of 12 mg/kg/day and in rabbits at doses of 10 mg/kg/day. Malaligned thoracic vertebrae were seen in rats at 36 mg/kg, a dose that produced maternal toxicity. These doses resulted in 2 times (rat at 12 mg/kg) or 5 times (rabbit at 10 mg/kg) the 40 mg human exposure based on mg/m^2 surface area. A study in which female rats were dosed during the third trimester at 12 and 24 mg/kg/day resulted in maternal mortality at or near term and postpartum. In addition, fetal and neonatal lethality were apparent. No effects on the dam or fetus occurred at 2 mg/kg/day. A second study at levels of 2, 6, 12 and 24 mg/kg/day confirmed the findings in the first study with neonatal mortality beginning at 6 mg/kg. A modified Segment III study was performed at dose levels of 12 or 24 mg/kg/day with or without the presence of concurrent supplementation with mevalonic acid, a product of HMG-CoA reductase which is essential for cholesterol biosynthesis. The concurrent administration of mevalonic acid completely prevented the maternal and neonatal mortality but did not prevent low body weights in pups at 24 mg/kg on Days 0 and 7 postpartum. Therefore, the maternal and neonatal lethality observed with fluvastatin sodium reflect its exaggerated pharmacologic effect during pregnancy. There are no data with fluvastatin sodium in pregnant women. However, rare reports of congenital anomalies have been received following intrauterine exposure to other HMG-CoA reductase inhibitors. There has been one report of severe congenital bony deformity, tracheo-esophageal fistula, and anal atresia (VATER association) in a baby born to a woman who took another HMG-CoA reductase inhibitor with dextroamphetamine sulfate during the first trimester of pregnancy. Lescol or Lescol XL should be administered to women of child-bearing potential only when such patients are highly unlikely to conceive and have been informed of the potential hazards. If a woman becomes pregnant while taking Lescol or Lescol XL, the drug should be discontinued and the patient advised again as to the potential hazards to the fetus.

Nursing Mothers

Based on preclinical data, drug is present in breast milk in a 2:1 ratio (milk:plasma). Because of the potential for serious adverse reactions in nursing infants, nursing women should not take Lescol or Lescol XL (see CONTRAINDICATIONS).

Pediatric Use

The safety and efficacy of Lescol and Lescol XL in children and adolescent patients 9-16 years of age with heterozygous familial hypercholesterolemia have been evaluated in open-label, uncontrolled clinical trials of 2 years' duration. The most common adverse events observed were influenza and infections. In these limited uncontrolled studies, there was no detectable effect on growth or sexual maturation in the adolescent boys or on menstrual cycle length in girls. See CLINICAL STUDIES: Heterozygous Familial Hypercholesterolemia in Pediatric Patients; ADVERSE REACTIONS: Pediatric Patients (9-16 years of age); and DOSAGE AND ADMINISTRATION: Heterozygous Familial Hypercholesterolemia in Pediatric Patients. Adolescent females should be counseled on appropriate contraceptive methods while on fluvastatin therapy (see CONTRAINDICATIONS: Pregnancy and Lactation).

Geriatric Use

The effect of age on the pharmacokinetics of immediate- release fluvastatin sodium was evaluated. Results indicate that for the general patient population plasma concentrations of fluvastatin sodium do not vary as a function of age. (See also CLINICAL PHARMACOLOGY: Pharmacokinetics/Metabolism.) Elderly patients (>65 years of age) demonstrated a greater treatment response in respect to LDL-C, Total-C and LDL/HDL ratio than patients <65 years of age.

ADVERSE REACTIONS

In all clinical studies of Lescol® (fluvastatin sodium), 1.0% (32/2969) of fluvastatin-treated patients were discontinued due to adverse experiences attributed to study drug (mean exposure approximately 16 months ranging in duration from 1 to >36 months). This results in an exposure adjusted rate of 0.8% (32/4051) per patient year in fluvastatin patients in controlled studies compared to an incidence of 1.1% (4/355) in placebo patients. Adverse reactions have usually been of mild to moderate severity.

In controlled clinical studies, 3.9% (36/912) of patients treated with Lescol® XL (fluvastatin sodium) 80 mg discontinued due to adverse events (causality not determined).

Clinically relevant adverse experiences occurring in the Lescol and Lescol XL controlled studies with a frequency >2%, regardless of causality, include the following:

Table 5 Clinically Relevant Adverse Experiences Occurring in >2% Patients in Lescol® and Lescol XL® Controlled Studies
 | Lescol®1 (%) | Placebo^1 (%) | Lescol® XL^2 (%)
Adverse Event | (N=2326) | (N=960) | (N = 912)
Musculoskeletal
Myalgia | 5.0 | 4.5 | 3.8
Arthritis | 2.1 | 2.0 | 1.3
Arthropathy | NA | NA | 3.2
Respiratory
Sinusitis | 2.6 | 1.9 | 3.5
Bronchitis | 1.8 | 1.0 | 2.6
Gastrointestinal
Dyspepsia | 7.9 | 3.2 | 3.5
Diarrhea | 4.9 | 4.2 | 3.3
Abdominal Pain | 4.9 | 3.8 | 3.7
Nausea | 3.2 | 2.0 | 2.5
Flatulence | 2.6 | 2.5 | 1.4
Psychiatric Disorders
Insomnia | 2.7 | 1.4 | 0.8
Genitourinary
Urinary Tract Infection | 1.6 | 1.1 | 2.7
Miscellaneous
Headache | 8.9 | 7.8 | 4.7
Influenza-Like Symptoms | 5.1 | 5.7 | 7.1
Accidental Trauma | 5.1 | 4.8 | 4.2
Fatigue | 2.7 | 2.3 | 1.6
Allergy | 2.3 | 2.2 | 1.0

^1 Controlled trials with Lescol Capsules (20 and 40 mg daily and 40 mg twice daily)

^2 Controlled trials with Lescol XL 80 mg Tablets

The following effects have been reported with drugs in this class. Not all the effects listed below have necessarily been associated with fluvastatin sodium therapy.

Skeletal: muscle cramps, myalgia, myopathy, rhabdomyolysis, arthralgias.

Neurological: dysfunction of certain cranial nerves (including alteration of taste, impairment of extra-ocular movement, facial paresis), tremor, dizziness, vertigo, memory loss, paresthesia, peripheral neuropathy, peripheral nerve palsy, psychic disturbances, anxiety, insomnia, depression.

Hypersensitivity Reactions: An apparent hypersensitivity syndrome has been reported rarely which has included one or more of the following features: anaphylaxis, angioedema, lupus erythematosus-like syndrome, polymyalgia rheumatica, vasculitis, purpura, thrombocytopenia, leukopenia, hemolytic anemia, positive ANA, ESR increase, eosinophilia, arthritis, arthralgia, urticaria, asthenia, photosensitivity, fever, chills, flushing, malaise, dyspnea, toxic epidermal necrolysis, erythema multiforme, including Stevens-Johnson syndrome.

Gastrointestinal: pancreatitis, hepatitis, including chronic active hepatitis, cholestatic jaundice, fatty change in liver, and, rarely, cirrhosis, fulminant hepatic necrosis, and hepatoma; anorexia, vomiting.

Skin: alopecia, pruritus. A variety of skin changes (e.g., nodules, discoloration, dryness of skin/mucous membranes, changes to hair/nails) have been reported.

Reproductive: gynecomastia, loss of libido, erectile dysfunction.

Eye: progression of cataracts (lens opacities), ophthalmoplegia.

Laboratory Abnormalities: elevated transaminases, alkaline phosphatase, γ-glutamyl transpeptidase, and bilirubin; thyroid function abnormalities.

Pediatric Patients

In two open-label, uncontrolled studies, 114 patients (66 boys and 48 girls) with heterozygous familial hypercholesterolemia, 9-16 years of age, were treated for 2 years with fluvastatin sodium administered as Lescol capsules 20 mg- 40 mg bid or Lescol XL 80 mg extended-release tablets. The most common adverse events observed were influenza and infections. (See CLINICAL STUDIES: Heterozygous Familial Hyercholesterolemia in Pediatric Patients and PRECAUTIONS: Pediatric Use).

Concomitant Therapy

Fluvastatin sodium has been administered concurrently with cholestyramine and nicotinic acid. No adverse reactions unique to the combination or in addition to those previously reported for this class of drugs alone have been reported. Myopathy and rhabdomyolysis (with or without acute renal failure) have been reported when another HMG-CoA reductase inhibitor was used in combination with immunosuppressive drugs, gemfibrozil, erythromycin, or lipid-lowering doses of nicotinic acid. Concomitant therapy with HMG-CoA reductase inhibitors and these agents is generally not recommended. (See WARNINGS: Skeletal Muscle.)

OVERDOSAGE

The approximate oral LD50 is greater than 2 g/kg in mice and greater than 0.7 g/kg in rats.

The maximum single oral dose of Lescol® (fluvastatin sodium) capsules received by healthy volunteers was 80 mg. No clinically significant adverse experiences were seen at this dose. The maximum dose administered with an extended-release formulation was 640 mg for two weeks. This dose was not well tolerated and produced a variety of GI complaints and an increase in transaminase values (i.e., SGOT and SGPT).

There has been a single report of 2 children, one 2 years old and the other 3 years of age, either of whom may have possibly ingested fluvastatin sodium. The maximum amount of fluvastatin sodium that could have been ingested was 80 mg (4 x 20 mg capsules). Vomiting was induced by ipecac in both children and no capsules were noted in their emesis. Neither child experienced any adverse symptoms and both recovered from the incident without problems.

Should an accidental overdose occur, treat symptomatically and institute supportive measures as required. The dialyzability of fluvastatin sodium and of its metabolites in humans is not known at present.

Information about the treatment of overdose can often be obtained from a certified Regional Poison Control Center. Telephone numbers of certified Regional Poison Control Centers are listed in the Physicians’ Desk Reference®.*

DOSAGE AND ADMINISTRATION

The patient should be placed on a standard cholesterol-lowering diet before receiving Lescol® (fluvastatin sodium) or Lescol® XL (fluvastatin sodium) and should continue on this diet during treatment with Lescol or Lescol XL. (See NCEP Treatment Guidelines for details on dietary therapy.)

For patients requiring LDL-C reduction to a goal of ≥25%, the recommended starting dose is 40 mg as one capsule in the evening, 80 mg as one Lescol XL tablet administered as a single dose at any time of the day or 80 mg in divided doses of the 40 mg capsule given twice daily. For patients requiring LDL-C reduction to a goal of <25% a starting dose of 20 mg may be used. The recommended dosing range is 20-80 mg/day. Lescol or Lescol XL may be taken without regard to meals, since there are no apparent differences in the lipid-lowering effects of fluvastatin sodium administered with the evening meal or 4 hours after the evening meal. Do not break, crush or chew Lescol XL tablets or open Lescol capsules prior to administration.

Since the maximal reductions in LDL-C of a given dose are seen within 4 weeks, periodic lipid determinations should be performed and dosage adjustment made according to the patient’s response to therapy and established treatment guidelines. The therapeutic effect of Lescol or Lescol XL is maintained with prolonged administration.

Heterozygous Familial Hypercholesterolemia in Pediatric Patients

The recommended starting dose is one 20 mg Lescol capsule. Dose adjustments, up to a maximum daily dose administered either as Lescol capsules 40 mg twice daily or one Lescol XL 80 mg tablet once daily, should be made at 6 week intervals. Doses should be individualized according to the goal of therapy (see NCEP Pediatric Panel Guidelines and INDICATIONS AND USAGE.)^1.

Concomitant Therapy

Lipid-lowering effects on total cholesterol and LDL cholesterol are additive when immediate release Lescol is combined with a bile-acid binding resin or niacin. When administering a bile-acid resin (e.g., cholestyramine) and fluvastatin sodium, Lescol should be administered at bedtime, at least 2 hours following the resin to avoid a significant interaction due to drug binding to resin. (See also ADVERSE REACTIONS: Concomitant Therapy.)

Dosage in Patients with Renal Insufficiency

Since fluvastatin sodium is cleared hepatically with less than 6% of the administered dose excreted into the urine, dose adjustments for mild to moderate renal impairment are not necessary. Fluvastatin has not been studied at doses greater than 40 mg in patients with severe renal impairment; therefore caution should be exercised when treating such patients at higher doses.

HOW SUPPLIED

Lescol® (fluvastatin sodium) Capsules 20 mg

Brown and light brown imprinted twice with " " and “20” on one half and “LESCOL” and the Lescol® (fluvastatin sodium) logo twice on the other half of the capsule.

Bottles of 30 | NDC 54868-3329-0

40 mg

Brown and gold imprinted twice with " " and “40” on one half and “LESCOL” and the Lescol® (fluvastatin sodium) logo twice on the other half of the capsule.

Bottles of 30 | NDC 54868-4224-0
Bottles of 60 | NDC 54868-4224-1

Store and Dispense

Store at 25ºC (77ºF); excursions permitted to 15 -30ºC (59 -86ºF) [see USP Controlled Room Temperature]. Dispense in a tight container. Protect from light.

REFERENCES

1. National Cholesterol Education Program (NCEP): Highlights of the Report of the Expert Panel on Blood Cholesterol Levels in Children and Adolescents. Pediatrics. 89(3):495-501.1992.

*Trademark Thomas Healthcare,, Inc.

REV: OCTOBER 2006 T2006-97

PATIENT INFORMATION

LESCOL® [ lĕs-cŏl]

(fluvastatin sodium)

Capsules

and

LESCOL® [ lĕs-cŏl] XL

(fluvastatin sodium)

Extended-Release Tablets

Rx only

Read the Patient Information that comes with LESCOL or LESCOL XL before you start taking it, and each time you get a refill. There may be new information. This leaflet does not take the place of talking with your doctor about your condition or treatment.

If you have any questions about LESCOL or LESCOL XL, ask your doctor or pharmacist.

What are LESCOL and LESCOL XL?

LESCOL and LESCOL XL are prescription medicines called "statins" that lower cholesterol in your blood. They lower the "bad" cholesterol and triglycerides in your blood. They can raise your "good" cholesterol as well.

LESCOL and LESCOL XL are for people whose cholesterol does not come down enough with exercise and a low-fat diet alone.

LESCOL and LESCOL XL may be used in patients with heart disease (coronary artery disease) to:

- lower the chances of heart problems which would require procedures to help restore blood flow to the heart.
- slow the buildup of too much cholesterol in the arteries of the heart.

Treatment with LESCOL or LESCOL XL has not been shown to prevent heart attacks or stroke.

LESCOL and LESCOL XL have the same active ingredient, fluvastatin. However, LESCOL is a capsule that is taken one or two times a day and LESCOL XL is an extended-release tablet that is only taken one time a day.

Who should not take LESCOL or LESCOL XL?

Do not take LESCOL or LESCOL XL if you:

- are pregnant or think you may be pregnant, or are planning to become pregnant. LESCOL and LESCOL XL may harm your unborn baby. If you get pregnant, stop taking LESCOL or LESCOL XL and call your doctor right away.
- are breast-feeding. LESCOL and LESCOL XL can pass into your breast milk and may harm your baby

- have liver problems
- are allergic to LESCOL or LESCOL XL or any of its ingredients. The active ingredient in LESCOL and LESCOL XL is fluvastatin. See the end of this leaflet for a complete list of ingredients in LESCOL and LESCOL XL.

LESCOL and LESCOL XL have not been studied in children under 9 years of age.

Before taking LESCOL or LESCOL XL, tell your doctor if you:

- have muscle aches or weakness
- drink more than 2 glasses of alcohol daily
- have diabetes
- have a thyroid problem
- have kidney problems

Some medicines should not be taken with LESCOL or LESCOL XL. Tell your doctor about all the medicines you take, including prescription and non-prescription medicines, vitamins and herbal supplements. LESCOL and LESCOL XL and certain other medicines can interact causing serious side effects. Especially tell your doctor if you take medicines for:

- your immune system
- cholesterol
- infections
- heart failure
- seizures
- diabetes
- heartburn or stomach ulcers

Know all the medicines you take. Keep a list of all the medicines you take with you to show your doctor and pharmacist.

How should I take LESCOL or LESCOL XL?

- Take LESCOL or LESCOL XL exactly as prescribed. Your doctor will prescribe the one that is right for you. Do not change your dose or stop LESCOL or LESCOL XL without talking to your doctor. Your doctor may do blood tests to check your cholesterol levels during treatment with LESCOL and LESCOL XL. Your dose of LESCOL or LESCOL XL may be changed based on these blood test results.

- LESCOL XL tablets may be taken at any time of the day. Take LESCOL capsules at the same time every evening. When LESCOL capsules are taken twice daily, the capsules may be taken once in the morning and once in the evening. LESCOL and LESCOL XL can be taken with or without food.

- LESCOL XL tablets must be swallowed whole with a liquid. Do not break, crush or chew LESCOL XL tablets or open Lescol capsules. Tell your doctor if you cannot swallow tablets whole. You may need LESCOL capsules or a different medicine instead of LESCOL XL tablets.

- Your doctor should start you on a low-fat and low-cholesterol diet before giving you LESCOL or LESCOL XL. Stay on this low-fat and low-cholesterol diet while taking LESCOL or LESCOL XL.
- If you miss a dose of LESCOL or LESCOL XL, take it as soon as you remember. Do not take Lescol or Lescol XL if it has been more than 12 hours since your last dose. Wait and take the next dose at your regular time. Do not take 2 doses of Lescol or Lescol XL at the same time.
- If you take too much LESCOL or LESCOL XL or overdose, call your doctor or Poison Control Center right away. Or, go to the nearest emergency room.

What should I avoid while taking LESCOL or LESCOL XL?

- Talk to your doctor before you start any new medicines. This includes prescription and nonprescription medicines, vitamins and herbal supplements. LESCOL and LESCOL XL and certain other medicines can interact causing serious side effects.
- Do not get pregnant. If you get pregnant, stop taking LESCOL or LESCOL XL right away and call your doctor.

What are the possible side effects of LESCOL and LESCOL XL?

When taking LESCOL and LESCOL XL, some patients may develop serious side effects, including:

- muscle problems. These serious muscle problems can sometimes lead to kidney problems, including kidney failure. You have a higher chance for muscle problems if you are taking certain other medicines with LESCOL or LESCOL XL.
- liver problems. Your doctor may do blood tests to check your liver before you start taking LESCOL or LESCOL XL, and while you are taking one of them.

Call your doctor right away if you have:

- muscle problems like weakness, tenderness, or pain that happen without a good reason, especially if you also have a fever or feel more tired than usual
- nausea and vomiting
- passing brown or dark-colored urine
- you feel more tired than usual
- your skin and whites of your eyes get yellow
- stomach pain

The most common side effects of LESCOL or LESCOL XL are headache, upset stomach and stomach pain, diarrhea, flu-like symptoms, muscle pain, sinus infection, tiredness, or trouble sleeping. These side effects are usually mild and may go away.

Talk to your doctor or pharmacist if you have side effects that bother you or that will not go away.

These are not all the side effects of LESCOL and LESCOL XL. Ask your doctor or pharmacist for a complete list.

How should I store LESCOL and LESCOL XL?

- Store LESCOL and LESCOL XL at room temperature, 59° to 86° F (15° to 30° C). Protect from light.
- Do not keep medicine that is out of date or that you no longer need.
- Keep LESCOL and LESCOL XL out of the reach of children. Be sure that if you throw medicines away, it is out of the reach of children.

General information about LESCOL and LESCOL XL

Medicines are sometimes prescribed for conditions that are not mentioned in patient information leaflets. Do not use LESCOL or LESCOL XL for a condition for which it was not prescribed. Do not give LESCOL or LESCOL XL to other people, even if they have the same problem you have. It may harm them.

This leaflet summarizes the most important information about LESCOL and LESCOL XL. If you would like more information, talk with your doctor.

For information that is written for health professionals, ask your doctor or pharmacist or call 1-888-669-6682.

What are the ingredients in LESCOL and LESCOL XL?

Active Ingredient: fluvastatin sodium

Inactive Ingredients:

LESCOL Capsules: gelatin, magnesium stearate, microcrystalline cellulose, pregelatinized starch (corn), red iron oxide, sodium lauryl sulfate, talc, titanium dioxide, yellow iron oxide, and other ingredients. The capsules may also contain benzyl alcohol, black iron oxide, butylparaben, carboxymethylcellulose sodium, edetate calcium disodium, methylparaben, propylparaben, silicon dioxide, and sodium propionate.

LESCOL XL Tablets: microcrystalline cellulose, hydroxypropyl cellulose, hydroxypropyl methylcellulose, potassium bicarbonate, povidone, magnesium stearate, yellow iron oxide, titanium dioxide and polyethylene glycol 8000.

Novartis Pharmaceuticals Corporation

East Hanover, New Jersey 07936

Rev: April 2006 T2006-50

Distributed by:

Novartis Pharmaceuticals Corporation

East Hanover, New Jersey 07936

REV: OCTOBER 2006 PRINTED IN THE U.S.A. T2006-97/T2006-50

5001004

5001006

Relabeling and Repackaging by:
Physicians Total Care, Inc.
Tulsa, OK 74146

PRINCIPAL DISPLAY PANEL

Package Label – 20 mg

Rx Only

Lescol® (fluvastatin sodium) capsules

equivalent to 20 mg fluvastatin

Package Label – 40 mg

Rx Only

Lescol® (fluvastatin sodium) capsules

equivalent to 40 mg fluvastatin